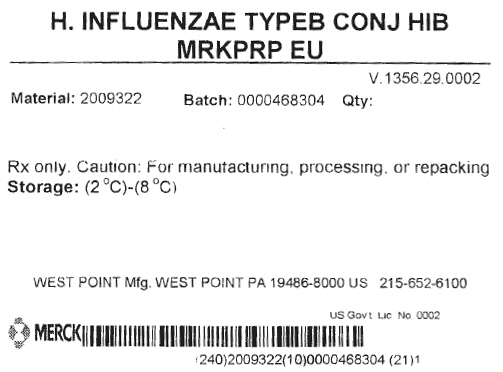 DRUG LABEL: Haemophilus Influenzae Type B Conjugate Hib
NDC: 69806-0001 | Form: LIQUID
Manufacturer: Merck Sharp & Dohme Corp.
Category: other | Type: LICENSED VACCINE BULK INTERMEDIATE LABEL
Date: 20150805

ACTIVE INGREDIENTS: HAEMOPHILUS INFLUENZAE TYPE B CAPSULAR POLYSACCHARIDE MENINGOCOCCAL OUTER MEMBRANE PROTEIN CONJUGATE ANTIGEN 1 g/1 g

H. INFLUENZAE TYPEB CONJ HIB MRKPRP EU

PRINCIPAL DISPLAY PANEL - Shipping Label

H. INFLUENZAE TYPEB CONJ HIB
MRKPRP EU

V.1356.29.0002

Material: 2009322
Batch: 0000468304
Qty:

Rx only. Caution: For manufacturing, processing, or repacking
Storage: (2 °C)-(8 °C)

WEST POINT Mfg. WEST POINT PA 19486-8000 US 215-652-6100

US Gov't Lic No. 0002

MERCK